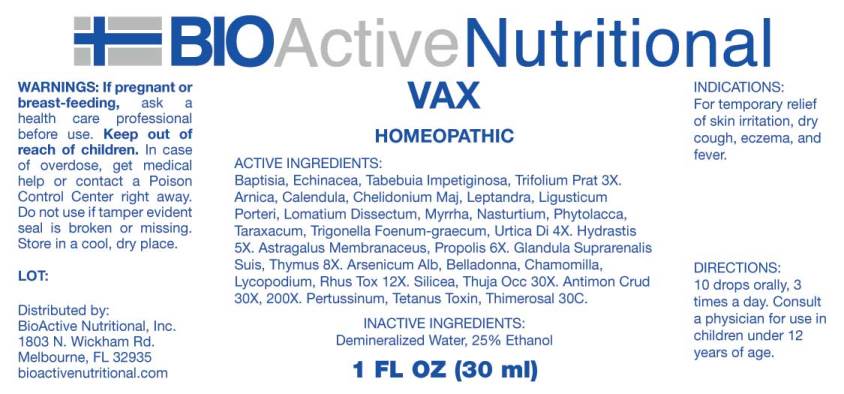 DRUG LABEL: VAX
NDC: 43857-0453 | Form: LIQUID
Manufacturer: BioActive Nutritional, Inc.
Category: homeopathic | Type: HUMAN OTC DRUG LABEL
Date: 20170720

ACTIVE INGREDIENTS: BAPTISIA TINCTORIA 3 [hp_X]/1 mL; ECHINACEA ANGUSTIFOLIA 3 [hp_X]/1 mL; TABEBUIA IMPETIGINOSA BARK 3 [hp_X]/1 mL; TRIFOLIUM PRATENSE FLOWER 3 [hp_X]/1 mL; ARNICA MONTANA 4 [hp_X]/1 mL; CALENDULA OFFICINALIS FLOWERING TOP 4 [hp_X]/1 mL; CHELIDONIUM MAJUS 4 [hp_X]/1 mL; VERONICASTRUM VIRGINICUM ROOT 4 [hp_X]/1 mL; LIGUSTICUM PORTERI ROOT 4 [hp_X]/1 mL; LOMATIUM DISSECTUM ROOT 4 [hp_X]/1 mL; MYRRH 4 [hp_X]/1 mL; NASTURTIUM OFFICINALE 4 [hp_X]/1 mL; PHYTOLACCA AMERICANA ROOT 4 [hp_X]/1 mL; TARAXACUM OFFICINALE 4 [hp_X]/1 mL; FENUGREEK SEED 4 [hp_X]/1 mL; URTICA DIOICA 4 [hp_X]/1 mL; GOLDENSEAL 5 [hp_X]/1 mL; ASTRAGALUS PROPINQUUS ROOT 6 [hp_X]/1 mL; PROPOLIS WAX 6 [hp_X]/1 mL; SUS SCROFA ADRENAL GLAND 8 [hp_X]/1 mL; SUS SCROFA THYMUS 8 [hp_X]/1 mL; ARSENIC TRIOXIDE 12 [hp_X]/1 mL; ATROPA BELLADONNA 12 [hp_X]/1 mL; CHAMOMILE 12 [hp_X]/1 mL; LYCOPODIUM CLAVATUM SPORE 12 [hp_X]/1 mL; TOXICODENDRON PUBESCENS LEAF 12 [hp_X]/1 mL; SILICON DIOXIDE 30 [hp_X]/1 mL; THUJA OCCIDENTALIS LEAFY TWIG 30 [hp_X]/1 mL; ANTIMONY TRISULFIDE 30 [hp_X]/1 mL; BORDETELLA PERTUSSIS 30 [hp_C]/1 mL; TETANUS TOXIN 30 [hp_C]/1 mL; THIMEROSAL 30 [hp_C]/1 mL
INACTIVE INGREDIENTS: WATER; ALCOHOL

Drug Facts:

ACTIVE INGREDIENTS:

Baptisia Tinctoria 3X, Echinacea (Angustifolia) 3X, Tabebuia Impetiginosa 3X, Trifolium Pratense 3X, Arnica Montana 4X, Calendula Officinalis 4X, Chelidonium Majus 4X, Leptandra Virginica 4X, Ligusticum Porteri 4X, Lomatium Dissectum 4X, Myrrha 4X, Nasturtium Aquaticum 4X, Phytolacca Decandra 4X, Taraxacum Officinale 4X, Trigonella Foenum-Graecum 4X, Urtica Dioica 4X, Hydrastis Canadensis 5X, Astragalus Membranaceus 6X, Propolis 6X, Glandula Suprarenalis Suis 8X, Thymus (Suis) 8X, Arsenicum Album 12X, Belladonna 12X, Chamomilla 12X, Lycopodium Clavatum 12X, Rhus Tox 12X, Silicea 30X, Thuja Occidentalis 30X, Antimonium Crudum 30X, 200X, Pertussinum 30C, Tetanus Toxin 30X, Thimerosal 30C.

INDICATIONS:

For temporary relief of skin irritation, dry cough, eczema, and fever.

WARNINGS:

If pregnant or breast-feeding, ask a health care professional before use.

Keep out of reach of children. In case of overdose, get medical help or contact a Poison Control Center right away.

Do not use if tamper evident seal is broken or missing.

Store in cool, dry place.

Keep out of reach of children. In case of overdose, get medical help or contact a Poison Control Center right away.

DIRECTIONS:

10 drops orally, 3 times a day. Consult a physician for use in children under 12 years of age.

INDICATIONS:

For temporary relief of skin irritation, dry cough, eczema, and fever.

INACTIVE INGREDIENTS:

Demineralized Water, 25% Ethanol.

QUESTIONS:

Distributed by:

BioActive Nutritional, Inc.

1803 N. Wickham Rd.

Melbourne, FL 32935

bioactivenutritional.com

PACKAGE LABEL DISPLAY:

BIOActive Nutritional

VAX

HOMEOPATHIC

1 FL OZ (30 ml)